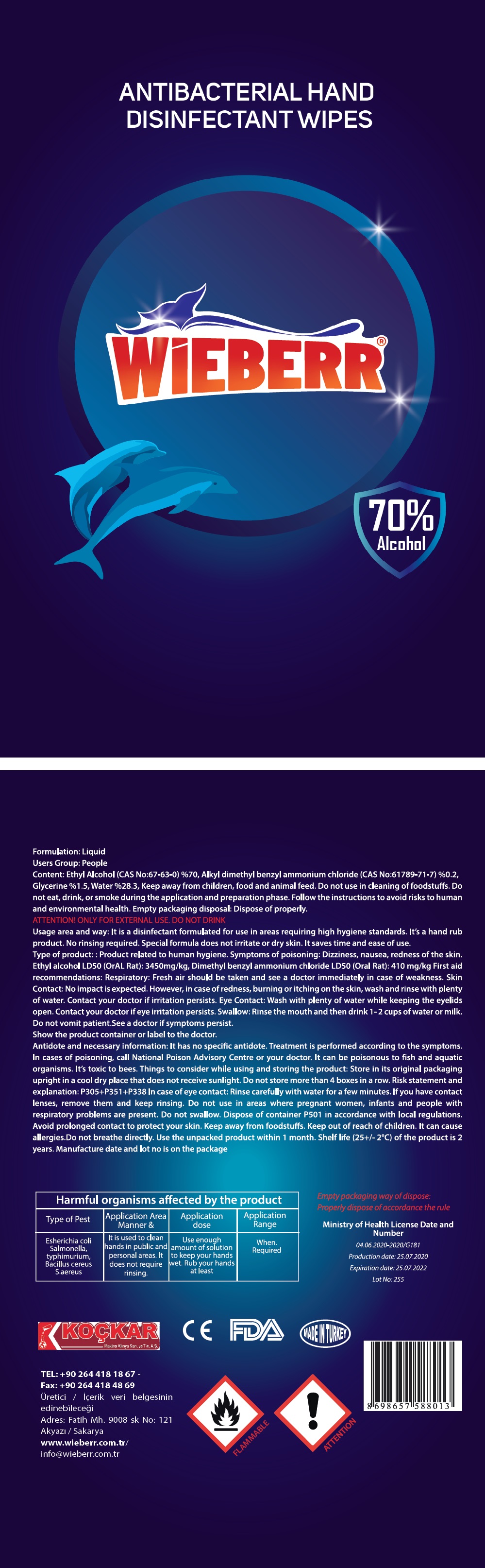 DRUG LABEL: Antibacterial Hand Disinfectant Wipes
NDC: 78433-301 | Form: CLOTH
Manufacturer: KOCKAR MAKINA KIMYA SANAYI VE TICARET ANONIM SIRKETI
Category: otc | Type: HUMAN OTC DRUG LABEL
Date: 20200722

ACTIVE INGREDIENTS: ALCOHOL 70 mL/100 g
INACTIVE INGREDIENTS: BENZALKONIUM CHLORIDE; GLYCERIN; WATER

WIEBERR® ANTIBACTERIAL HAND DISINFECTANT WIPES

Active ingredient: Ethyl Alcohol (CAS No:67-63-0) %70

Purpose: Antiseptic

INDICATIONS AND USAGE

Uses: Usage area and way: It is a disinfectant formulated for use in areas requiring high hygiene standards.

It's a hand rub product. No rinsing required. Special formula does not irritate or dry skin. It saves time

and ease of use.

WARNINGS

Warnings: Symptoms of poisoning: Dizziness, nausea, redness of the skin. Ethyl alcohol LD50 (OrAL Rat):

3450mg/kg, Dimethyl benzyl ammonium chloride LD50 (OraL Rat): 410mg/kg First aid recommendations:

Respiratory: Fresh air should be taken and see a doctor immediately in case of weakness. Skin Contact:

No impact is expected. However, in case of redness, burning or itching on the skin, wash and rinse with

plenty of water. Contact your doctor if irritation persists. Eye contact: Wash with plenty of water while

keeping the eyelids open. Contact your doctor if eye irritation persists. Swallow: Rinse the mouth and

then drink 1-2 cups of water or milk. Do not vomit patient. see a doctor if symptoms persist.

Show the product container or label to the doctor.

Antidote and necessary information: It has no specific antidote. Treatment is performed according to

the symptoms. In cases of poisoning, call National Poison Advisory Centre or your doctor. It can be

poisonous to fish and aquatic organisms. It's toxic to bees.

Risk statement and explanation: p305+P351+P338 In case of eye contact: Rinse carefully with water for a few

minutes. If you have contact lenses, remove them and keep rinsing. Do not use in areas where pregnant women,

infants and people with respiratory problems are present. Do not swallow.

Avoid prolonged contact to protect your skin. Keep away from foodstuffs.

Do not breathe directly.

Keep out of reach of children. It can cause allergies.

Directions:

Harmful organisms affected by the product
Type of Pest | Application Area Manner & | Application dose | Application Range
Esherichia coli Salmonella, typhi murium, Bacillus cereus S.aereus. | It is used to clean hands in public and personal areas. It does not require rinsing. | Use enough amount of solution to keep your hands wet. Rub your hands at least | When. Required.

STORAGE AND HANDLING

Other informations: Things to consider while using and storing the product: Store in its original

packaging upright in a cool dry place that does not receive sunlight.

Do not store more than 4 boxes in a row.

Dispose of container P501 in accordance with local regulations.

Use the unpacked product within 1 month. Shelf life (25+/-2°C) of the product is 2 years.

INACTIVE INGREDIENT

Content: Ethyl Alcohol (CAS No:67-63-0) %70, Alkyl dimethyl benzyl ammonium chloride

(CAS No:61789-71-7) %0.2, Glycerine %1.5, Water %28.3.

70% Alcohol

Formulation: Liquid

Users Group: People

Keep away from children, food and animal feed. Do not use in cleaning of foodstuffs. Do not eat, drink,

or smoke during the application and preparation phase. Follow the instructions to avoid risks to human

and environmental health. Empty packaging disposal: Dispose of properly.

ATTENTION! ONLY FOR EXTERNAL USE. DO NOT DRINK

Type of product: Product related to human hygiene.

Manufacture date and lot no is on the package.

Empty packaging way of dispose: Properly dispose of accordance the rule.

Ministry of Health License Date and Number

04.06.2020-2020/G181

Production date: 25.07.2020

Expiration date: 25.07.2022

KOCKAR

Makina Kimya san. ve Tic. A. S.

TEL: +90 264 418 18 67 -

Fax: +90 264 418 48 69

Adres: Fatih Mh. 9008 Sk. No:121

Akyazi / Sakarya

www.wieberr.com.tr /

info@wieberr.com.tr

MADE IN TURKEY